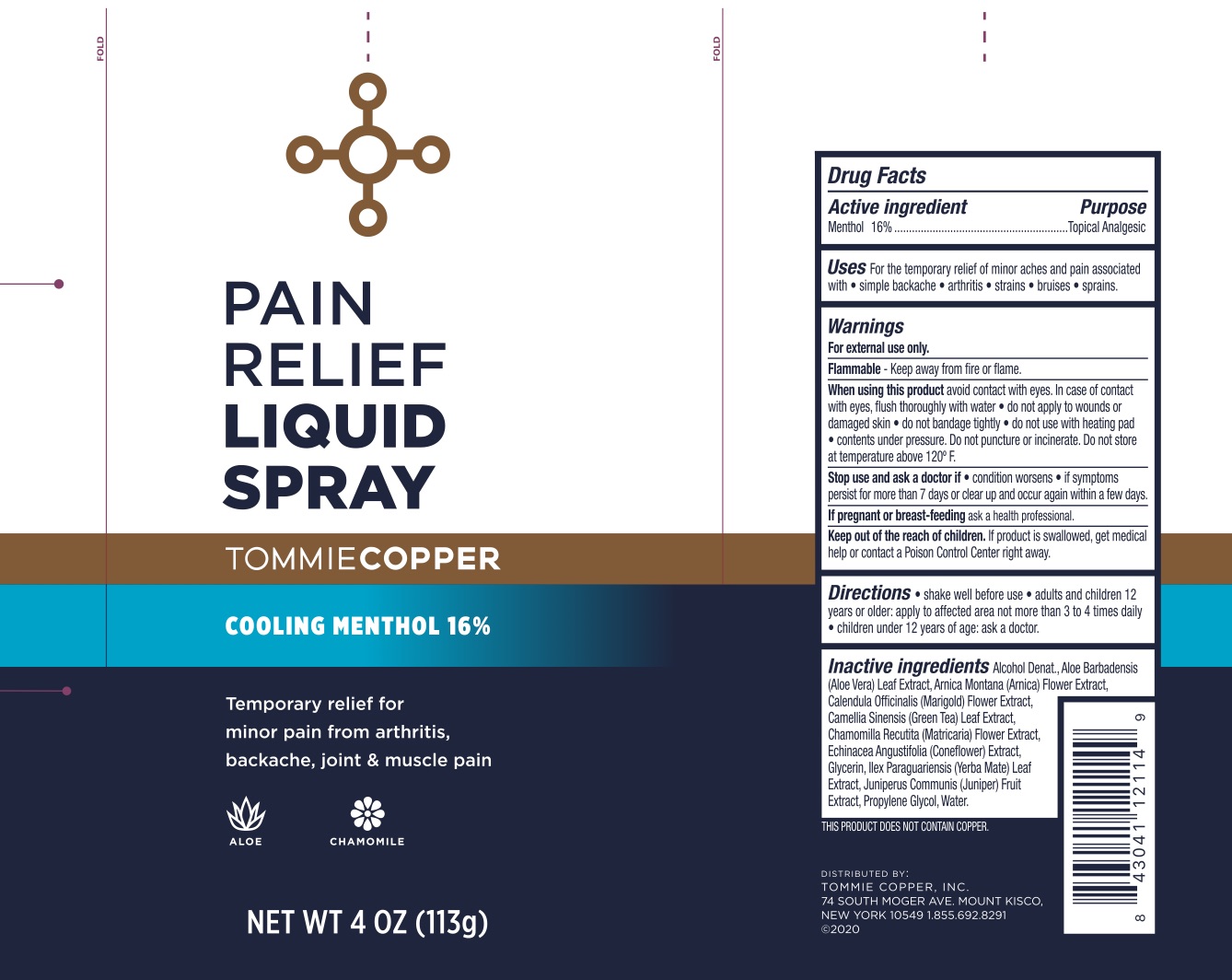 DRUG LABEL: Tommie Copper Pain Relief
NDC: 72562-910 | Form: SPRAY
Manufacturer: Tommie Copper, Inc.
Category: otc | Type: HUMAN OTC DRUG LABEL
Date: 20241215

ACTIVE INGREDIENTS: MENTHOL 16 g/100 g
INACTIVE INGREDIENTS: CALENDULA ARVENSIS LEAF; PROPYLENE GLYCOL; WATER; GLYCERIN; ALOE VERA LEAF; ALCOHOL; ILEX PARAGUARIENSIS LEAF; MATRICARIA CHAMOMILLA FLOWERING TOP OIL; ECHINACEA ANGUSTIFOLIA; ARNICA MONTANA FLOWER; JUNIPER BERRY; GREEN TEA LEAF

Pain Relief Liquid Spray

ACTIVE INGREDIENT

Menthol 16%

PURPOSE

Topical Analgesic

INDICATIONS AND USAGE

For the temporary relief of minor aches and pain associated with simple backaches, arthritis, strains, bruises, and sprains.

WARNINGS

For external use only. Flammable--Keep away from fire or flame. When using this product avoid contact with eyes. In case of contact with eyes, flush thoroughly with water, do not apply to wounds or damaged skin, and do not bandage tightly, do not use with a heating pad. Contents under pressure. Do not puncture or incinerate. Do not store at temperature above 120F. . Stop use and ask a doctor if condition worsens, if symptoms persist for more than 7 days or clear up and occur again within a few days.

PREGNANCY OR BREAST FEEDING

If pregnant or breast-feeding ask a health professional.

KEEP OUT OF REACH OF CHILDREN

If swallowed, get medical help or contact a Poison Control Center right away.

DOSAGE AND ADMINISTRATION

Shake well before use. Adults and children 12 years of age and older, apply to the affected area not more than 3 to 4 times daily. Children under 12 years of age: ask a doctor.

INACTIVE INGREDIENT

Alcohol Denat., Aloe Barbadensis (Aloe Vera) Leaf Extract, Arnica Montana (Arnica) Flower Extract, Calendula Officinalis (Marigold) Flower Extract, Camellia Sinensis (Green Tea) Leaf Extract, Echinacea Angustifolia (Coneflower) Extract, Glycerin, Ilex Paraguariensis (Yerba Mate) Leaf Extract, Juniperus Communis (Juniper) Fruit Extract, Propylene Glycol, Water